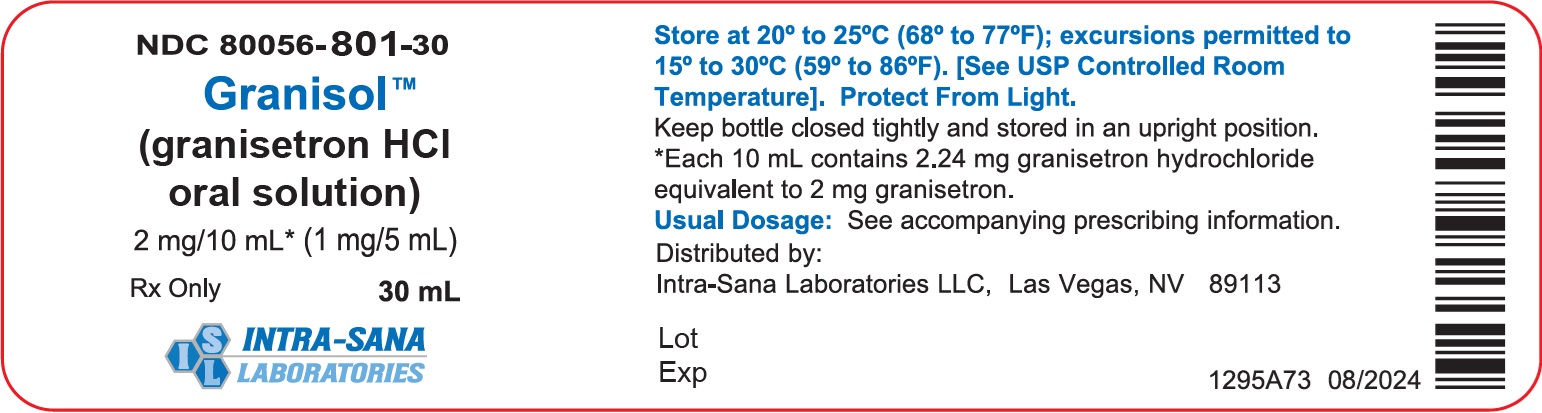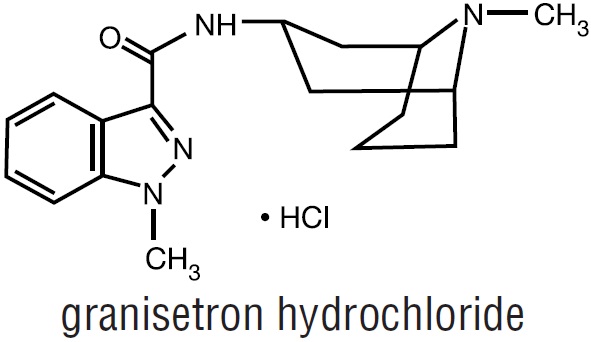 DRUG LABEL: Granisol
NDC: 80056-801 | Form: SOLUTION
Manufacturer: Intra-Sana Laboratories
Category: prescription | Type: HUMAN PRESCRIPTION DRUG LABEL
Date: 20250321

ACTIVE INGREDIENTS: GRANISETRON HYDROCHLORIDE 2 mg/10 mL
INACTIVE INGREDIENTS: ANHYDROUS CITRIC ACID; FD&C YELLOW NO. 6; WATER; SODIUM BENZOATE; SORBITOL

DESCRIPTION

GRANISOL™ oral solution contains granisetron hydrochloride, an antinauseant and antiemetic agent. Chemically it is endo-N-(9-methyl-9-azabicyclo [3.3.1] non-3-yl)-1-methyl-1H-indazole-3-carboxamide hydrochloride with a molecular weight of 348.9 (312.4 free base). Its empirical formula is C18H24N4O•HCl, while its chemical structure is:

Granisetron hydrochloride is a white to off-white solid that is readily soluble in water and normal saline at 20°C.

Oral Solution

Each 10 mL of clear, orange-colored, orange-flavored GRANISOL™ oral solution contains 2.24 mg of granisetron hydrochloride equivalent to 2 mg granisetron. Inactive ingredients: citric acid anhydrous, FD&C Yellow No. 6, orange flavor, purified water, sodium benzoate, and sorbitol.

CLINICAL PHARMACOLOGY

Granisetron is a selective 5-hydroxytryptamine3 (5-HT3) receptor antagonist with little or no affinity for other serotonin receptors, including 5-HT1; 5-HT1A; 5-HT1B/C; 5-HT2; for alpha1-, alpha2-, or beta-adrenoreceptors; for dopamine-D2; or for histamine-H1; benzodiazepine; picrotoxin or opioid receptors.

Serotonin receptors of the 5-HT3 type are located peripherally on vagal nerve terminals and centrally in the chemoreceptor trigger zone of the area postrema. During chemotherapy that induces vomiting, mucosal enterochromaffin cells release serotonin, which stimulates 5-HT3 receptors. This evokes vagal afferent discharge, inducing vomiting. Animal studies demonstrate that, in binding to 5-HT3 receptors, granisetron blocks serotonin stimulation and subsequent vomiting after emetogenic stimuli such as cisplatin. In the ferret animal model, a single granisetron injection prevented vomiting due to high-dose cisplatin or arrested vomiting within 5 to 30 seconds.

In most human studies, granisetron has had little effect on blood pressure, heart rate or ECG. No evidence of an effect on plasma prolactin or aldosterone concentrations has been found in other studies.

Following single and multiple oral doses, Kytril tablets slowed colonic transit in normal volunteers. However, granisetron had no effect on oro-cecal transit time in normal volunteers when given as a single intravenous (IV) infusion of 50 mcg/kg or 200 mcg/kg.

Pharmacokinetics

In healthy volunteers and adult cancer patients undergoing chemotherapy, administration of Kytril tablets produced mean pharmacokinetic data shown in Table 1.

Table 1 Pharmacokinetic Parameters (Median [range]) Following Kytril Tablets
 | Peak Plasma Concentration; (ng/mL) | Terminal Phase Half-Life; (h) | Volume of Distribution; (L/kg) | Total Clearance; (L/h/kg)
Cancer Patients; 1 mg bid, 7 days; (n=27) | 5.99; [0.63 to 30.9] | N.D.^1 | N.D. | 0.52; [0.09 to 7.37]
Volunteers; Single 1 mg dose; (n=39) | 3.63; [0.27 to 9.14] | 6.23; [0.96 to 19.9] | 3.94; [1.89 to 39.4] | 0.41; [0.11 to 24.6]
^1Not determined after oral administration; following a single intravenous dose of 40 mcg/kg, terminal phase half-life was determined to be 8.95 hours.
N.D. Not determined.

A 2 mg dose of GRANISOL oral solution is bioequivalent to the corresponding dose of Kytril tablets (1 mg x 2) and may be used interchangeably.

Absorption

When Kytril tablets were administered with food, AUC was decreased by 5% and Cmaxincreased by 30% in non-fasted healthy volunteers who received a single dose of 10 mg.

Distribution

Plasma protein binding is approximately 65% and granisetron distributes freely between plasma and red blood cells.

Metabolism

Granisetron metabolism involves N-demethylation and aromatic ring oxidation followed by conjugation. In vitro liver microsomal studies show that granisetron's major route of metabolism is inhibited by ketoconazole, suggestive of metabolism mediated by the cytochrome P-450 3A subfamily. Animal studies suggest that some of the metabolites may also have 5-HT3 receptor antagonist activity.

Elimination

Clearance is predominantly by hepatic metabolism. In normal volunteers, approximately 11% of the orally administered dose is eliminated unchanged in the urine in 48 hours. The remainder of the dose is excreted as metabolites, 48% in the urine and 38% in the feces.

Subpopulations

Gender

The effects of gender on the pharmacokinetics of Kytril tablets have not been studied. However, after intravenous infusion of granisetron, no difference in mean AUC was found between males and females, although males had a higher Cmax generally.

In elderly and pediatric patients and in patients with renal failure or hepatic impairment, the pharmacokinetics of granisetron was determined following administration of intravenous Kytril.

Elderly

The ranges of the pharmacokinetic parameters in elderly volunteers (mean age 71 years), given a single 40-mcg/kg intravenous dose of Kytril injection, were generally similar to those in younger healthy volunteers; mean values were lower for clearance and longer for half-life in the elderly.

Renal Failure Patients

Total clearance of granisetron was not affected in patients with severe renal failure who received a single 40 mcg/kg intravenous dose of Kytril injection.

Hepatically Impaired Patients

A pharmacokinetic study with intravenous Kytril in patients with hepatic impairment due to neoplastic liver involvement showed that total clearance was approximately halved compared to patients without hepatic impairment. Given the wide variability in pharmacokinetic parameters noted in patients, dosage adjustment in patients with possible hepatic functional impairment is not necessary.

Pediatric Patients

A pharmacokinetic study in pediatric cancer patients (2 to 16 years of age), given a single 40 mcg/kg intravenous dose of Kytril injection, showed that volume of distribution and total clearance increased with age. No relationship with age was observed for peak plasma concentration or terminal phase plasma half-life. When volume of distribution and total clearance are adjusted for body weight, the pharmacokinetics of granisetron are similar in pediatric and adult cancer patients.

CLINICAL TRIALS

Chemotherapy-Induced Nausea and Vomiting

Kytril tablets prevent nausea and vomiting associated with initial and repeat courses of emetogenic cancer therapy, as shown by 24-hour efficacy data from studies using both moderately- and highly-emetogenic chemotherapy.

Moderately Emetogenic Chemotherapy

The first trial compared Kytril tablets doses of 0.25 mg to 2 mg twice a day, in 930 cancer patients receiving, principally, cyclophosphamide, carboplatin, and cisplatin (20 mg/m^2 to 50 mg/m^2). Efficacy was based on complete response (i.e., no vomiting, no moderate or severe nausea, no rescue medication), no vomiting, and no nausea. Table 2 summarizes the results of this study.

Table 2 Prevention of Nausea and Vomiting 24 Hours Post-Chemotherapy^1
Percentages of Patients
Kytril Tablet Dose
Efficacy Measures | 0.25 mg twice a day; (n=229); % | 0.5 mg twice a day; (n=235); % | 1 mg twice a day; (n=233); % | 2 mg twice a day; (n=233); %
Complete Response^2 | 61 | 70* | 81*^+ | 72*
No Vomiting | 66 | 77* | 88* | 79*
No Nausea | 48 | 57 | 63* | 54
^1Chemotherapy included oral and injectable cyclophosphamide, carboplatin, cisplatin (20 mg/m^2 to 50 mg/m^2), dacarbazine, doxorubicin, epirubicin.
^2No vomiting, no moderate or severe nausea, no rescue medication.
* Statistically significant (P < 0.01) vs. 0.25 mg twice a day.
^+ Statistically significant (P < 0.01) vs. 0.5 mg twice a day.

Results from a second double-blind, randomized trial evaluating Kytril tablets 2 mg once a day and Kytril tablets 1 mg twice a day were compared to prochlorperazine 10 mg twice a day derived from a historical control. At 24 hours, there was no statistically significant difference in efficacy between the two Kytril tablet regimens. Both regimens were statistically superior to the prochlorperazine control regimen (see Table 3).

Table 3 Prevention of Nausea and Vomiting 24 Hours Post-Chemotherapy^1
Percentage of Patients
Efficacy Measures | Kytril Tablets; 1 mg twice a day; (n=354); % | Kytril Tablets; 2 mg once a day; (n=343); % | Prochlorperazine^2; 10 mg twice daily; (n=111); %
Complete Response^3 | 69* | 64* | 41
No Vomiting | 82* | 77* | 48
No Nausea | 51* | 53* | 35
Total Control^4 | 51* | 50* | 33
^1Moderately emetogenic chemotherapeutic agents included cisplatin (20 mg/m^2 to 50 mg/m^2), oral and intravenous cyclophosphamide, carboplatin, dacarbazine, doxorubicin.
^2Historical control from a previous double-blind granisetron trial.
^3No vomiting, no moderate or severe nausea, no rescue medication.
^4No vomiting, no nausea, no rescue medication.
* Statistically significant (P < 0.05) vs. prochlorperazine historical control.

Results from a Kytril tablets 2 mg daily alone treatment arm in a third double-blind, randomized trial, were compared to prochlorperazine (PCPZ), 10 mg bid, derived from a historical control. The 24-hour results for Kytril tablets 2 mg daily were statistically superior to PCPZ for all efficacy parameters: complete response (58%), no vomiting (79%), no nausea (51%), total control (49%). The PCPZ rates are shown in Table 3.

Cisplatin-Based Chemotherapy

The first double-blind trial compared Kytril tablets 1 mg bid, relative to placebo (historical control), in 119 cancer patients receiving high-dose cisplatin (mean dose 80 mg/m2). At 24 hours, Kytril tablets 1 mg bid was significantly (P < 0.001) superior to placebo (historical control) in all efficacy parameters: complete response (52%), no vomiting (56%) and no nausea (45%). The placebo rates were 7%, 14%, and 7%, respectively, for the three efficacy parameters.

Results from a Kytril 2 mg once a day alone treatment arm in a second double-blind, randomized trial, were compared to both Kytril tablets 1 mg twice a day and placebo historical controls. The 24-hour results for Kytril 2 mg once a day were: complete response (44%), no vomiting (58%), no nausea (46%), total control (40%). The efficacy of Kytril tablets 2 mg once a day was comparable to tablets 1 mg twice a day and statistically superior to placebo. The placebo rates were 7%, 14%, 7%, and 7%, respectively, for the four parameters.

No controlled study comparing granisetron injection with the oral formulation to prevent chemotherapy-induced nausea and vomiting has been performed.

Radiation-Induced Nausea and Vomiting

Total Body Irradiation

In a double-blind randomized study, 18 patients receiving Kytril tablets, 2 mg daily, experienced significantly greater antiemetic protection compared to patients in a historical negative control group who received conventional (non-5-HT3 antagonist) antiemetics. Total body irradiation consisted of 11 fractions of 120 cGy administered over 4 days, with three fractions on each of the first 3 days, and two fractions on the fourth day. Kytril tablets were given one hour before the first radiation fraction of each day.

Twenty-two percent (22%) of patients treated with Kytril tablets did not experience vomiting or receive rescue antiemetics over the entire 4-day dosing period, compared to 0% of patients in the historical negative control group (P < 0.01).

In addition, patients who received Kytril tablets also experienced significantly fewer emetic episodes during the first day of radiation and over the 4-day treatment period, compared to patients in the historical negative control group. The median time to the first emetic episode was 36 hours for patients who received Kytril tablets.

Fractionated Abdominal Radiation

The efficacy of Kytril tablets, 2 mg daily, was evaluated in a double-blind, placebo-controlled randomized trial of 260 patients. Kytril tablets were given 1 hour before radiation, composed of up to 20 daily fractions of 180 to 300 cGy each. The exceptions were patients with seminoma or those receiving whole abdomen irradiation who initially received 150 cGy per fraction. Radiation was administered to the upper abdomen with a field size of at least 100 cm^2.

The proportion of patients without emesis and those without nausea for Kytril tablets, compared to placebo, was statistically significant (P < 0.0001) at 24 hours after radiation, irrespective of the radiation dose. Granisetron was superior to placebo in patients receiving up to 10 daily fractions of radiation, but was not superior to placebo in patients receiving 20 fractions.

Patients treated with Kytril tablets (n=134) had a significantly longer time to the first episode of vomiting (35 days vs. 9 days, P < 0.001) relative to those patients who received placebo (n=126), and a significantly longer time to the first episode of nausea (11 days vs. 1 day, P < 0.001). Granisetron provided significantly greater protection from nausea and vomiting than placebo.

INDICATIONS AND USAGE

Granisetron is indicated for the prevention of:

- Nausea and vomiting associated with initial and repeat courses of emetogenic cancer therapy, including high-dose cisplatin.
- Nausea and vomiting associated with radiation, including total body irradiation and fractionated abdominal radiation.

CONTRAINDICATIONS

Granisetron is contraindicated in patients with known hypersensitivity to the drug or any of its components.

WARNINGS

Serotonin Syndrome

The development of serotonin syndrome has been reported with 5-HT3 receptor antagonists alone but particularly with concomitant use of serotonergic drugs (e.g., selective serotonin reuptake inhibitors (SSRIs), serotonin and norepinephrine reuptake inhibitors (SNRIs), monoamine oxidase inhibitors, mirtazapine, fentanyl, lithium, tramadol, and intravenous methylene blue). Some of the reported cases were fatal. Serotonin syndrome occurring with overdose of another 5-HT3 receptor antagonist alone has also been reported. The majority of reports of serotonin syndrome related to 5-HT3 receptor antagonist use occurred in a post-anesthesia care unit or an infusion center.

Symptoms associated with serotonin syndrome may include mental status changes (e.g., agitation, hallucinations, delirium, and coma), autonomic instability (e.g., tachycardia, labile blood pressure, dizziness, diaphoresis, flushing, hyperthermia), neuromuscular symptoms (e.g., tremor, rigidity, myoclonus, hyperreflexia, incoordination), seizures, and/or gastrointestinal symptoms (e.g., nausea, vomiting, diarrhea). Patients should be monitored for the emergence of serotonin syndrome, especially with concomitant use of granisetron and other serotonergic drugs. If symptoms of serotonin syndrome occur, discontinue granisetron and initiate supportive treatment. Patients should be informed of the increased risk of serotonin syndrome, especially if granisetron is used concomitantly with other serotonergic drugs [see Drug Interactions].

PRECAUTIONS

Granisetron is not a drug that stimulates gastric or intestinal peristalsis. It should not be used instead of nasogastric suction. The use of granisetron in patients following abdominal surgery or in patients with chemotherapy-induced nausea and vomiting may mask a progressive ileus and/or gastric distention.

An adequate QT assessment has not been conducted, but QT prolongation has been reported with granisetron. Therefore, GRANISOL oral solution should be used with caution in patients with pre-existing arrhythmias or cardiac conduction disorders, as this might lead to clinical consequences. Patients with cardiac disease, on cardio-toxic chemotherapy, with concomitant electrolyte abnormalities and/or on concomitant medications that prolong the QT interval are particularly at risk.

Drug Interactions

Granisetron does not induce or inhibit the cytochrome P-450 drug-metabolizing enzyme system in vitro. There have been no definitive drug-drug interaction studies to examine pharmacokinetic or pharmacodynamic interaction with other drugs; however, in humans, Kytril injection has been safely administered with drugs representing benzodiazepines, neuroleptics, and anti-ulcer medications commonly prescribed with antiemetic treatments. Kytril injection also does not appear to interact with emetogenic cancer chemotherapies. Because granisetron is metabolized by hepatic cytochrome P-450 drug-metabolizing enzymes, inducers or inhibitors of these enzymes may change the clearance and, hence, the half-life of granisetron. No specific interaction studies have been conducted in anesthetized patients. In addition, the activity of the cytochrome P-450 subfamily 3A4 (involved in the metabolism of some of the main narcotic analgesic agents) is not modified by granisetron in vitro.

In in vitro human microsomal studies, ketoconazole inhibited ring oxidation of granisetron. However, the clinical significance of in vivo pharmacokinetic interactions with ketoconazole is not known. In a human pharmacokinetic study, hepatic enzyme induction with phenobarbital resulted in a 25% increase in total plasma clearance of intravenous granisetron. The clinical significance of this change is not known.

QT prolongation has been reported with granisetron. Use of GRANISOL oral solution in patients concurrently treated with drugs known to prolong the QT interval and/or are arrhythmogenic may result in clinical consequences.

Carcinogenesis, Mutagenesis, Impairment of Fertility

In a 24-month carcinogenicity study, rats were treated orally with granisetron 1, 5 or 50 mg/kg/day (6, 30 or 300 mg/m^2/day). The 50 mg/kg/day dose was reduced to 25 mg/kg/day (150 mg/m^2/day) during week 59 due to toxicity. For a 50 kg person of average height (1.46 m2 body surface area), these doses represent 4, 20, and 101 times the recommended clinical dose (1.48 mg/m^2, oral) on a body surface area basis. There was a statistically significant increase in the incidence of hepatocellular carcinomas and adenomas in males treated with 5 mg/kg/day (30 mg/m2/day, 20 times the recommended human dose based on body surface area) and above, and in females treated with 25 mg/kg/day (150 mg/m^2/day, 101 times the recommended human dose based on body surface area). No increase in liver tumors was observed at a dose of 1 mg/kg/day (6 mg/m^2/day, 4 times the recommended human dose based on body surface area) in males and 5 mg/kg/day (30 mg/m^2/day, 20 times the recommended human dose based on body surface area) in females. In a 12-month oral toxicity study, treatment with granisetron 100 mg/kg/day (600 mg/m^2/day, 405 times the recommended human dose based on body surface area) produced hepatocellular adenomas in male and female rats while no such tumors were found in the control rats. A 24-month mouse carcinogenicity study of granisetron did not show a statistically significant increase in tumor incidence, but the study was not conclusive.

Because of the tumor findings in rat studies, granisetron should be prescribed only at the dose and for the indication recommended (see INDICATIONS AND USAGE, and DOSAGE AND ADMINISTRATION).

Granisetron was not mutagenic in the in vitro Ames test and mouse lymphoma cell forward mutation assay, and in vivo mouse micronucleus test and in vitro and ex vivo rat hepatocyte UDS assays. It, however, produced a significant increase in UDS in HeLa cells in vitro and a significant increased incidence of cells with polyploidy in an in vitro human lymphocyte chromosomal aberration test.

Granisetron at oral doses up to 100 mg/kg/day (600 mg/m^2/day, 405 times the recommended human dose based on body surface area) was found to have no effect on fertility and reproductive performance of male and female rats.

Pregnancy

Teratogenic Effects

Pregnancy Category B

Reproduction studies have been performed in pregnant rats at oral doses up to 125 mg/kg/day (750 mg/m^2/day, 507 times the recommended human dose based on body surface area) and pregnant rabbits at oral doses up to 32 mg/kg/day (378 mg/m^2/day, 255 times the recommended human dose based on body surface area) and have revealed no evidence of impaired fertility or harm to the fetus due to granisetron. There are, however, no adequate and well-controlled studies in pregnant women. Because animal reproduction studies are not always predictive of human response, this drug should be used during pregnancy only if clearly needed.

Nursing Mothers

It is not known whether granisetron is excreted in human milk. Because many drugs are excreted in human milk, caution should be exercised when granisetron is administered to a nursing woman.

Pediatric Use

Safety and effectiveness in pediatric patients have not been established.

Geriatric Use

During clinical trials, 325 patients 65 years of age or older received Kytril tablets; 298 were 65 to 74 years of age, and 27 were 75 years of age or older. Efficacy and safety were maintained with increasing age.

ADVERSE REACTIONS

QT prolongation has been reported with granisetron (see PRECAUTIONSand Drug Interactions).

Chemotherapy-Induced Nausea and Vomiting

Over 3700 patients have received Kytril tablets in clinical trials with emetogenic cancer therapies consisting primarily of cyclophosphamide or cisplatin regimens.

In patients receiving Kytril tablets 1 mg bid for 1, 7 or 14 days, or 2 mg daily for 1 day, adverse experiences reported in more than 5% of the patients with comparator and placebo incidences are listed in Table 4.

Table 4 Principal Adverse Events in Clinical Trials
Percent of Patients With Event
 | Kytril^1 Tablets; 1 mg twice a day; (n=978) | Kytril^1 Tablets; 2 mg once a day; N=1450) | Comparator^2; (n=599) | Placebo; (n=185)
Headache^3 | 21% | 20% | 13% | 12%
Constipation | 18% | 14% | 16% | 8%
Asthenia | 14% | 18% | 10% | 45
Diarrhea | 8% | 9% | 10% | 4%
Abdominal Pain | 6% | 4% | 6% | 3%
Dyspepsia | 4% | 6% | 5% | 4%
^1Adverse events were recorded for 7 days when Kytril tablets were given on a single day and for up to 28 days when Kytril tablets were administered for 7 or 14 days.
^2Metoclopramide/dexamethasone; phenothiazines/dexamethasone; dexamethasone alone; prochlorperazine.
^3Usually mild to moderate in severity.

Other adverse events reported in clinical trials were:

Gastrointestinal: In single-day dosing studies in which adverse events were collected for 7 days, nausea (20%) and vomiting (12%) were recorded as adverse events after the 24-hour efficacy assessment period.

Hepatic: In comparative trials, elevation of AST and ALT (> 2 times the upper limit of normal) following the administration of Kytril tablets occurred in 5% and 6% of patients, respectively. These frequencies were not significantly different from those seen with comparators (AST: 2%; ALT: 9%).

Cardiovascular: Hypertension (1%); hypotension, angina pectoris, atrial fibrillation, and syncope have been observed rarely.

Central Nervous System: Dizziness (5%), insomnia (5%), anxiety (2%), somnolence (1%).

One case compatible with, but not diagnostic of, extrapyramidal symptoms has been reported in a patient treated with Kytril tablets.

Hypersensitivity: Rare cases of hypersensitivity reactions, sometimes severe (eg, anaphylaxis, shortness of breath, hypotension, urticaria) have been reported.

Other: Fever (5%). Events often associated with chemotherapy also have been reported: leukopenia (9%), decreased appetite (6%), anemia (4%), alopecia (3%), thrombocytopenia (2%).

Over 5000 patients have received injectable Kytril in clinical trials.

Table 5 gives the comparative frequencies of the five commonly reported adverse events (≥3%) in patients receiving Kytril injection, 40 mcg/kg, in single-day chemotherapy trials. These patients received chemotherapy, primarily cisplatin, and intravenous fluids during the 24-hour period following Kytril injection administration.

Table 5 Principal Adverse Events in Clinical Trials - Single-Day Chemotherapy
Percent of Patients With Event
 | Kytril Injection^1; 40 mcg/kg; (n=1268) | Comparator^2; (n=422)
Headache | 14% | 6%
Asthenia | 5% | 6%
Somnolence | 4% | 15%
Diarrhea | 4% | 6%
Constipation | 3% | 3%
^1Adverse events were generally recorded over 7 days post-Kytril injection administration.
^2Metoclopramide/dexamethasone and phenothiazines/dexamethasone.

OVERDOSAGE

There is no specific treatment for granisetron hydrochloride overdosage. In case of overdosage, symptomatic treatment should be given. Overdosage of up to 38.5 mg of granisetron hydrochloride injection has been reported without symptoms or only the occurrence of a slight headache.

DOSAGE AND ADMINISTRATION

Emetogenic Chemotherapy

The recommended adult dosage of oral granisetron hydrochloride is 2 mg once daily or 1 mg twice daily. In the 2 mg once-daily regimen, 10 mL of GRANISOL oral solution (2 teaspoonfuls, equivalent to 2 mg of granisetron) are given up to 1 hour before chemotherapy. In the 1 mg twice-daily regimen, the first teaspoonful (5 mL) of GRANISOL oral solution is given up to 1 hour before chemotherapy, and the second teaspoonful (5 mL) of GRANISOL oral solution, 12 hours after the first. Either regimen is administered only on the day(s) chemotherapy is given. Continued treatment, while not on chemotherapy, has not been found to be useful.

Use in the Elderly, Renal Failure Patients or Hepatically Impaired Patients

No dosage adjustment is recommended (see CLINICAL PHARMACOLOGY: Pharmacokinetics).

Pediatric Use

Safety and effectiveness in pediatric patients have not been established.

Radiation (Either Total Body Irradiation or Fractionated Abdominal Radiation)

The recommended adult dosage of oral granisetron hydrochloride is 2 mg once daily. Ten milliliters of GRANISOL oral solution (2 teaspoonfuls, equivalent to 2 mg of granisetron) are taken within 1 hour of radiation.

Pediatric Use

Safety and effectiveness in pediatric patients have not been established.

Use in the Elderly

No dosage adjustment is recommended.

HOW SUPPLIED

Oral Solution

Clear, orange-colored, orange-flavored, 2 mg/10 mL, in 30 mL amber glass bottles with child-resistant closures: NDC 80056-801-30

Storage

Store at 20° to 25°C (68° to 77°F); excursions permitted to 15° to 30°C (59° to 86°F).

[See USP Controlled Room Temperature]. Keep bottle closed tightly and stored in an upright position. Protect from light.

Distributed by Intra-Sana Laboratories LLC

Las Vegas, NV 89113